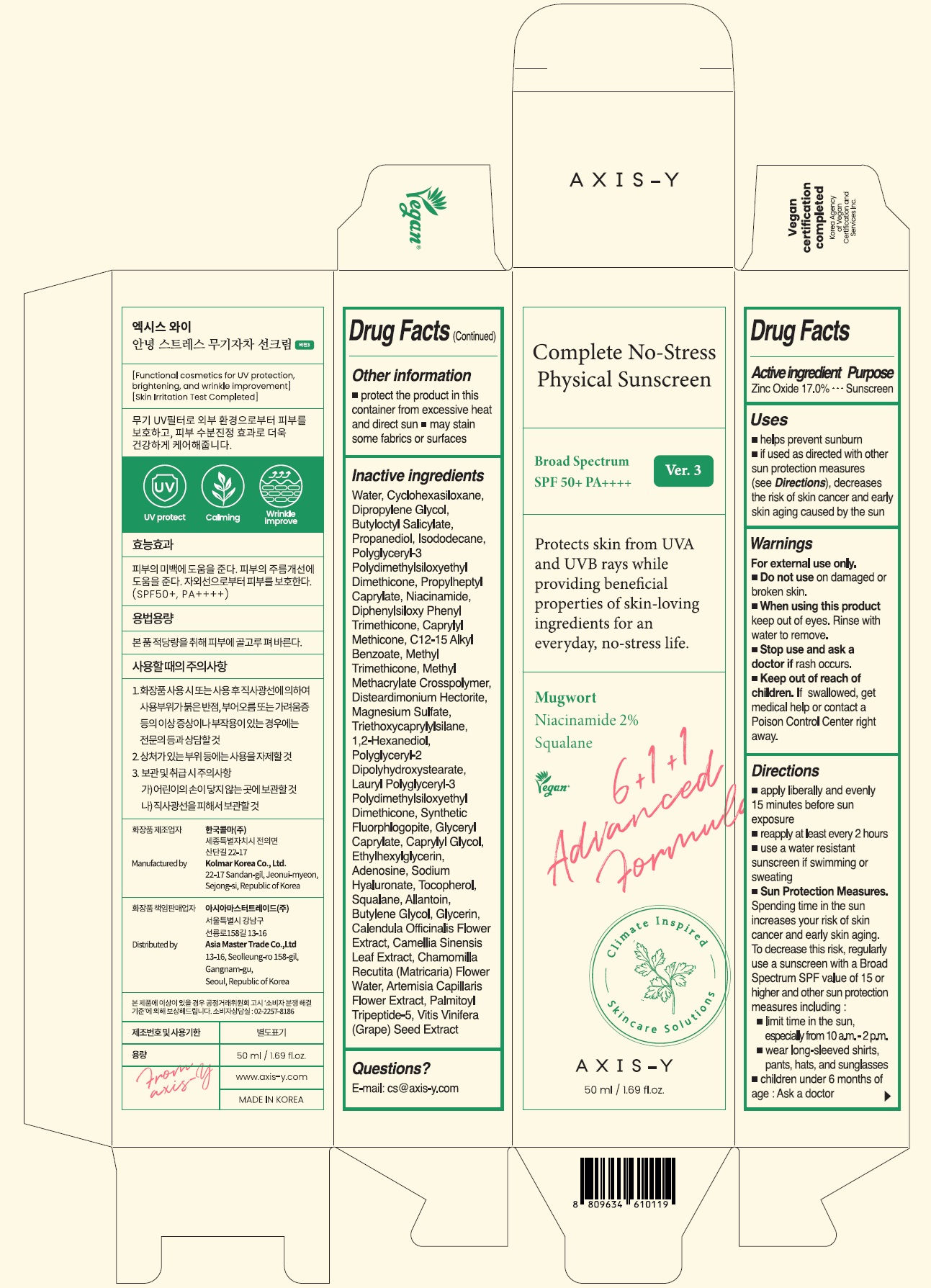 DRUG LABEL: AXIS-Y Complete No-Stress Physical Sunscreen V.3
NDC: 84467-101 | Form: CREAM
Manufacturer: Asia Master Trade Co.,Ltd
Category: otc | Type: HUMAN OTC DRUG LABEL
Date: 20241101

ACTIVE INGREDIENTS: ZINC OXIDE 17 g/50 mL
INACTIVE INGREDIENTS: WATER

AXIS-Y Complete No-Stress Physical Sunscreen Ver.3 Broad Spectrum SPF 50+ PA++++

Active Ingredient

Zinc Oxide 17.0%

Purpose

Sunscreen

Uses

- helps prevent sunburn
- if used as directed with other sun protection measures (see Directions), decreases the risk of skin cancer and early skin aging caused by the sun

Warnings

For external use only.

- Do not use on on damaged or broken skin.

- When using this product keep out of eyes. Rinse with water to remove.

- Stop use and ask a doctor if rash occurs.

- Keep out of reach of children. If swallowed, get medical help or contact a Poison Control Center right away.

Directions

- apply liberally 15 minutes before sun exposure
- reapply at least every 2 hours
- use a water resistant sunscreen if swimming or sweating
- Sun Protections Measures. Spending time in the sun increases your risk of skin cancer and early skin aging. To decrease this risk, regurlarly use a sunscreen with a BroadSpectrum SPF value of 15 or higher and other sun protection measures including:
- limit time in the sun, especially from 10 a.m. - 2 p.m.
- wear long-sleeved shirts, pants, hats, and sunglasses.

- children under 6 months of age: Ask a doctor

Other Information

- protect the product in this container from excessive heat and direct sun
- may stain some fabrics or surfaces

Inactive Ingredient

Water, Cyclohexasiloxane, Dipropylene Glycol, Butyloctyl Salicylate, Propanediol, Isododecane, Polyglyceryl-3 Polydimethylsiloxyethyl Dimethicone, Propylheptyl Caprylate, Niacinamide, Diphenylsiloxy Phenyl Trimethicone, Caprylyl Methicone, C12-15 Alkyl Benzoate, Methyl Trimethicone, Methyl Methacrylate Crosspolymer, Disteardimonium Hectorite, Magnesium Sulfate, Triethoxycaprylylsilane, 1,2-Hexanediol, Polyglyceryl-2 Dipolyhydroxystearate, Lauryl Polyglyceryl-3 Polydimethylsiloxyethyl Dimethicone, Synthetic Fluorophlogopite, Glyceryl Caprylate, Caprylyl Glycol, Ethylhexylglycerin, Adenosine, Sodium Hyaluronate, Tocopherol, Squalane, Allantoin, Butylene Glycol, Glycerin, Calendula Officinalis Flower Extract, Camellia Sinensis Leaf Extract, Chamomilla Recutita (Matricaria) Flower Water, Artemisia Capillaris Flower Extract, Palmitoyl Tripeptide-5, Vitis Vinifera (Grape) Seed Extract.

Questions?

E-mail: cs@axis-y.com

Distributed by

Asia Master Trade Co.,Ltd
13-16, Seolleung-ro 158-gil,
Gangnam-gu,
Seoul, Republic of Korea

Principal Display Panel

Complete No-Stress
Physical Sunscreen
Ver.3
Broad Spectrum
SPF 50+ PA++++
Protects skin from UVA
and UVB rays while
providing beneficial
properties of skin-loving
ingredients for an
everyday, no-stress life.
Mugwort
Niacinamide 2%
Squalane
Vegan
6+1+1
Advanced
Formula
Climate Inspired
Skincare Solutions
AXIS-Y
50ml / 1.69 fl.oz